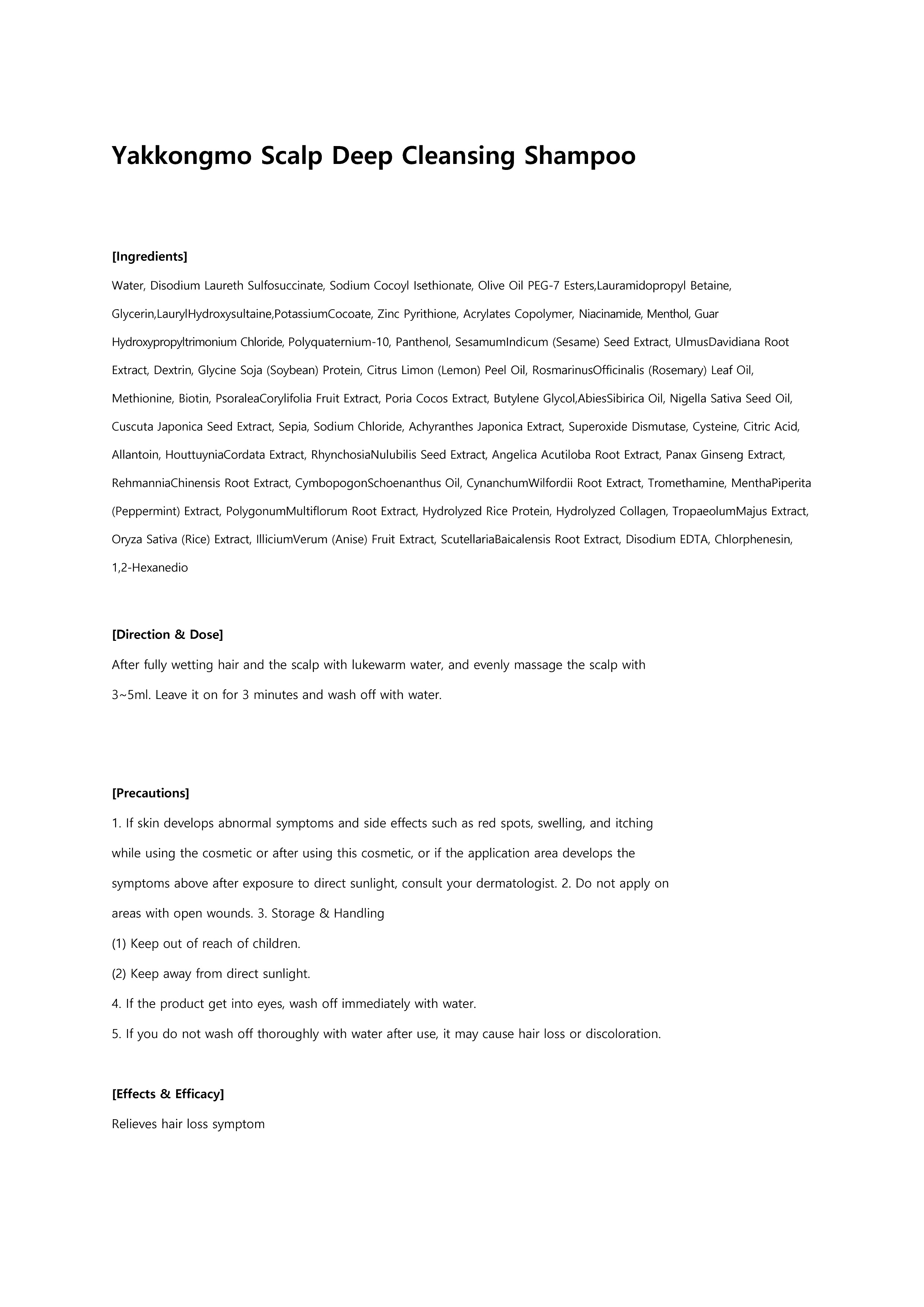 DRUG LABEL: Yakkongmo treatment
NDC: 73540-003 | Form: LIQUID
Manufacturer: BOBSNU CO., LTD.
Category: otc | Type: HUMAN OTC DRUG LABEL
Date: 20200222

ACTIVE INGREDIENTS: SALICYLIC ACID 0.2 g/100 mL; PYRITHIONE ZINC 0.6 g/100 mL; DEXPANTHENOL 0.5 g/100 mL
INACTIVE INGREDIENTS: WATER

ACTIVE INGREDIENT

zinc pyrithione, dexpanthenol, salicylic acid

INACTIVE INGREDIENT

Water, Dipropylene Glycol, Propylene Glycol, Glycerin, Cetyl Alcohol, Stearyl Alcohol, Glyceryl Stearate, Stearamidopropyl Dimethylamine, Behentrimonium Chloride, CetylEthylhexanoate, PPG-3 Caprylyl Ether, Steartrimonium Chloride, Panthenol, Citrus Limon (Lemon) Peel Oil, AnibaRosodora (Rosewood) Wood Oil, Caprylyl Glycol, Zinc Pyrithione, Salicylic Acid, Hydroxyethylcellulose, Citrus Reticulata (Tangerine) Peel Oil, Niacinamide, Butylene Glycol, Sodium Polynaphthalenesulfonate, 1,2-Hexanediol, Glycine, Glycine Max (Soybean) Seed Extract, VignaRadiata Seed Extract, ArchisHypogaea (Peanut) Fruit Extract, PisumSativum (Pea) Seed Extract, CanavaliaGladiata Extract, PhaseolusAngularis Seed Extract, SesamumIndicum (Sesame) Seed Extract, VacciniumAngustifolium (Blueberry) Fruit Extract, Salvia Hispanica Seed Extract, Nigella Sativa Seed Extract, RubusFruticosus (Blackberry) Fruit Extract, RibesNigrum (Black Currant) Fruit Extract, Oryza Sativa (Rice) Extract, Serine, Glutamic Acid, Aspartic Acid, Leucine, Alanine, Lysine, Arginine, Tyrosine, Phenylalanine, Valine, Threonine, Proline, Isoleucine, OenotheraBiennis (Evening Primrose) Flower Extract, UlmusDavidiana Root Extract, PinusPalustris Leaf Extract, PuerariaLobata Root Extract, Histidine, Methionine, Cysteine, Ethylhexylglycerin, Hydrolyzed Corn Protein, Hydrolyzed Wheat Protein, Hydrolyzed Soy Protein, Acacia Senegal Gum, Sodium Polynaphthalenesulfonate, Peat water, Citric Acid, Hydroxypropyl Methylcellulose, Potassium Sorbate

PURPOSE

Helps alleviate symptoms of hair loss

WARNINGS

1. If skin develops abnormal symptoms or side effects such as red spots, swelling, and itching while or after using the product, or if the application area develops the symptoms above after exposure to direct sunlight, consult your dermatologist. 2. Do not apply on areas with open wounds. 3. Storage & Handling (1). Keep out of reach of children. (2) Keep away from direct sunlight. 4. If the product gets into eyes, rinse immediately with water 5. If you do not rinse thoroughly with water after use, it may cause hair loss or discoloration.

Keep Out of Reach of Children

Directions

Use once a day as follows: 1) Fully wet hair and scalp with lukewarm water. 2) Dispense an appropriate amount in your palm and evenly apply on hair and scalp. 3) After 2-3 minutes, rinse with lukewarm water.

INDICATIONS AND USAGE

Helps alleviate symptoms of hair loss